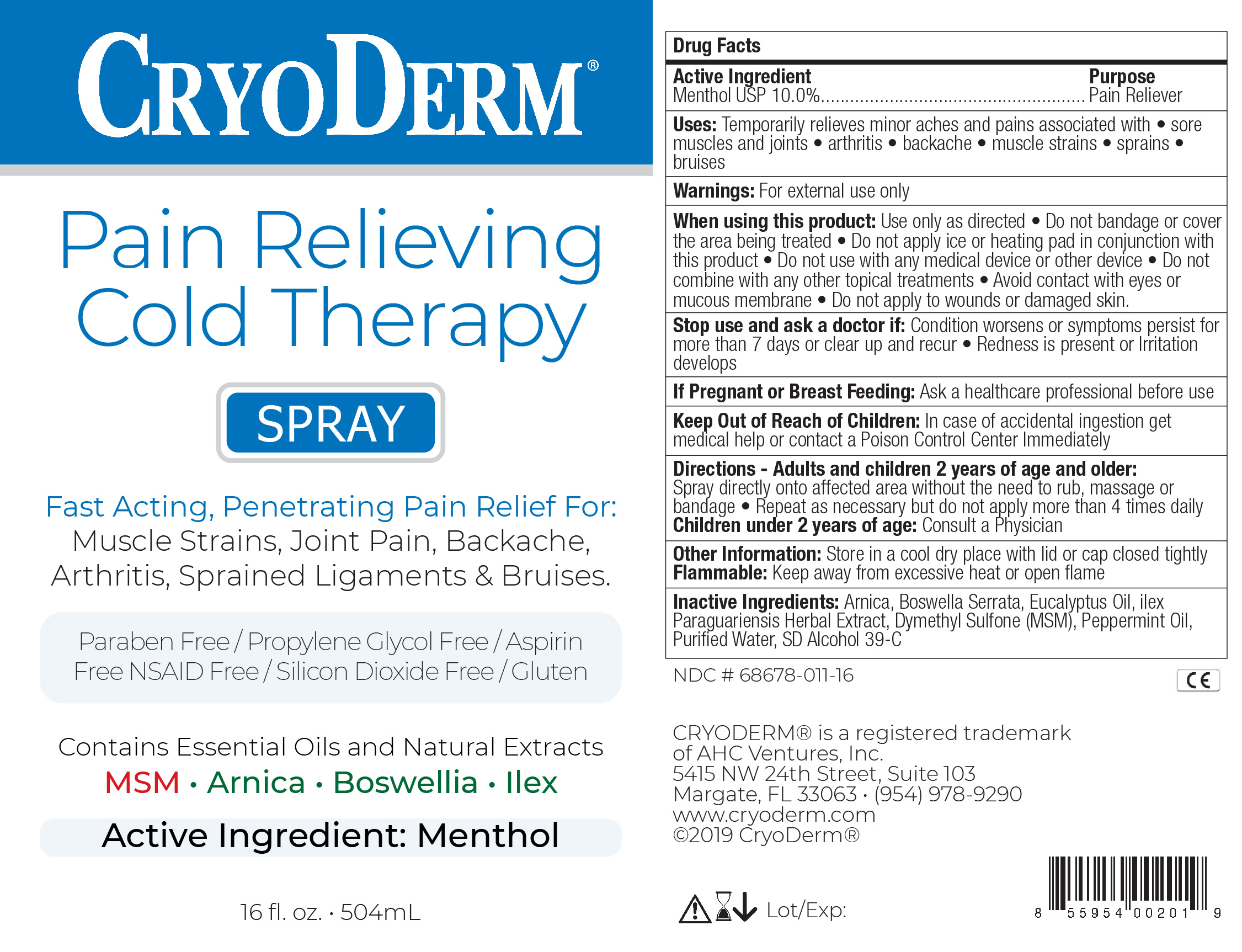 DRUG LABEL: Cold Therapy
NDC: 68678-012 | Form: SPRAY
Manufacturer: AHC Ventures Corp DBA Cryoderm
Category: otc | Type: HUMAN OTC DRUG LABEL
Date: 20250902

ACTIVE INGREDIENTS: MENTHOL 10 g/100 mL
INACTIVE INGREDIENTS: BOSWELLIA SERRATA WHOLE 1 mL/100 mL; EUCALYPTOL 0.05 mL/100 mL; ILEX PARAGUARIENSIS LEAF 1 mL/100 mL; ARNICA MONTANA FLOWER 1 mL/100 mL; DIMETHYL SULFONE 2 mL/100 mL; PEPPERMINT OIL 0.05 1/100 mL; WATER 33.5 1/100 mL; ALCOHOL 51.4 mg/100 mL

Cryoderm Cold Therapy Spray

Stop use and ask doctor if:

Condition worsens or symptoms persist for more than 7 days or clear up and recur. Redness is present or irritatio develops

Inactive Ingredients

Arnica, Boswella Serrata, Eucalyptus Oil, Ilex Paragariensis Leaf Extract, Dimethyl Sulfone (MSM), Prppermint Oil, Purified Wter, SD Alcohol 39-C

If Pregnant or Breast Feeding

Ask a healthcare professional before use

When using this product

Use only as directed. Do not bandage or use a heating pad or device. Avoid contact with eyes and mucous membranes. Do not apply to open wounds or damaged skin. Do not use with other ointmen

Active Ingredient

Menthol USP 10.0%

Uses

Temporary relieves minor aches and pains associated with

- sore muscles and joints
- arthritis
- backache
- muscle strains
- sprains
- bruises

Purpose

Pain Reliever

Warnings

For external use only

Keep Out Of Reach Of Children

In case of accidental ingestion get medical help or contact a Poison Control Center immediately

INSTRUCTIONS FOR USE

Adults and children 2 years and older:
Spray directly onto affected area without the need to rub, massage or bandage. Repeat as necessary but do not apply more than 4 times daily.
Children under 2 years of age: Consult a Physician

Inactive Ingredients

Arnica, Boswella Serrata, Eucalyptus Oil, Ilex Paragariensis Leaf Extract, Dimethyl Sulfone (MSM), Prppermint Oil, Purified Wter, SD Alcohol 39-C

PDP

CryoDerm

Pain Relieving Cold Therapy

Spray

Fast Acting, Penetrating Pain Relief for:

Muscle Strains, Joint Pain, Backache, Arthritis, Sprained Ligaments & Bruises

Contains Essential Oils and Natural Extracts

MSM Arnica Boswellia Ilex

Active Ingredient: Menthol

16 fl. oz. 504 mL